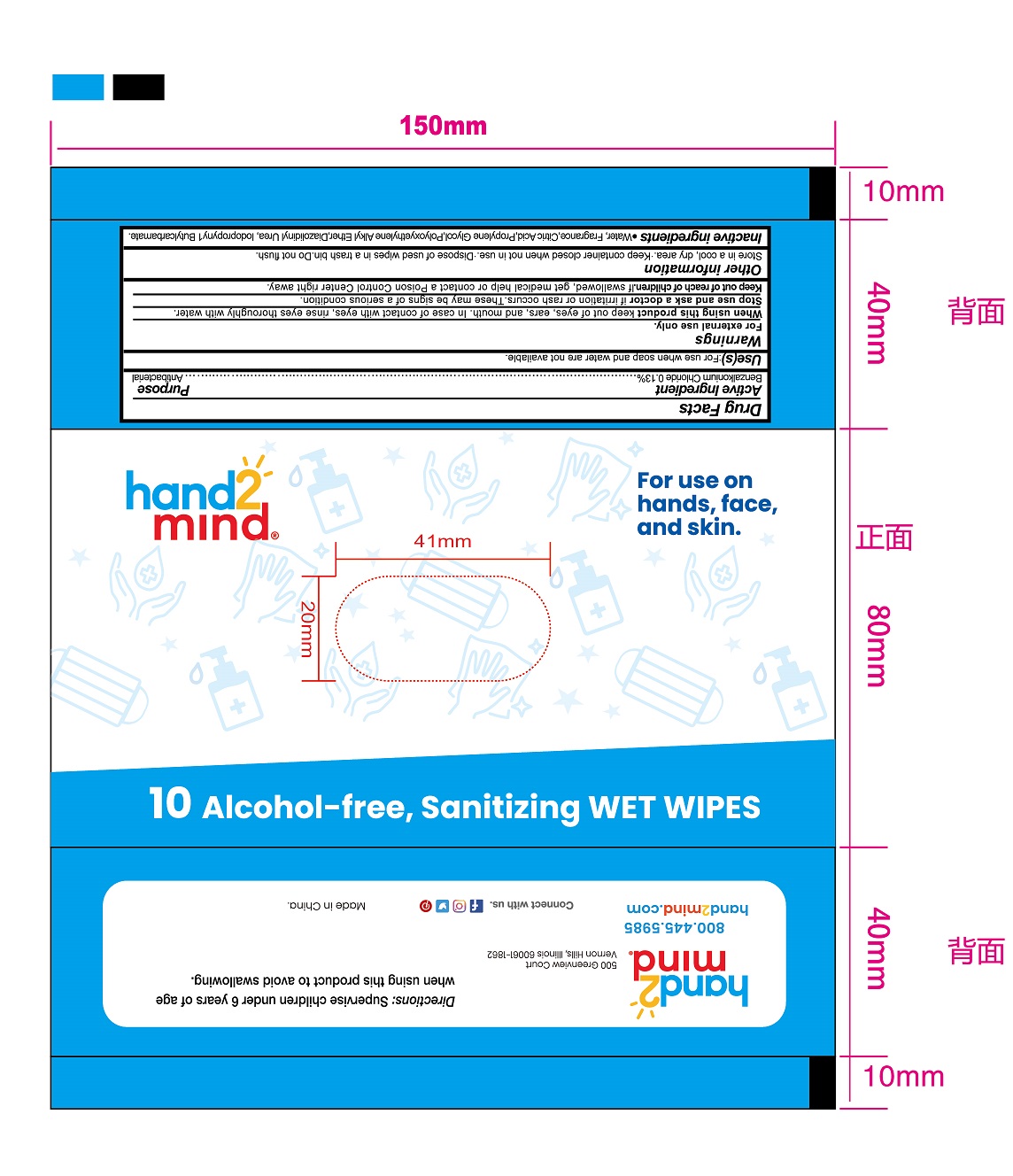 DRUG LABEL: hand2mind Sanitizing Wet Wipes
NDC: 80800-002 | Form: SOLUTION
Manufacturer: Taizhou Duorui Biotechnology Co., Ltd.
Category: otc | Type: HUMAN OTC DRUG LABEL
Date: 20210312

ACTIVE INGREDIENTS: BENZALKONIUM CHLORIDE 0.13 g/100 mL
INACTIVE INGREDIENTS: WATER; CITRIC ACID MONOHYDRATE; PROPYLENE GLYCOL; DIAZOLIDINYL UREA; IODOPROPYNYL BUTYLCARBAMATE

80800-002 wipes

Active Ingredient(s)

Benzalkonium Chloride 0.13%

Purpose

Antibacterial

Use

For use when soap and water are not available

Warnings

For external use only.

When using this product, keep out of eyes, ears or mouth. In case of contact with eyes, rinse eyes thoroughly with water.

Stop use and ask a doctor if irritation or rash occurs, these may be signs of a serious condition.

Keep out of reach of children. If swallowed, get immediate medical help or contact a Poison Control Center right away.

Directions

- Supervise children under 6 years of age when using this product to avoid swallowing

Other Information

Store in a cool, dry area. Keep container closed when not in use. Dispose of used wipes in trash bin. Do not flush.

Inactive ingredients

Water, Fragrance, Citric Acid, Propylene Glycol, Polyoxyethylene Alkyl Ether, Diazolidinyl Urea, Iodopropynyl Butylcarbamate